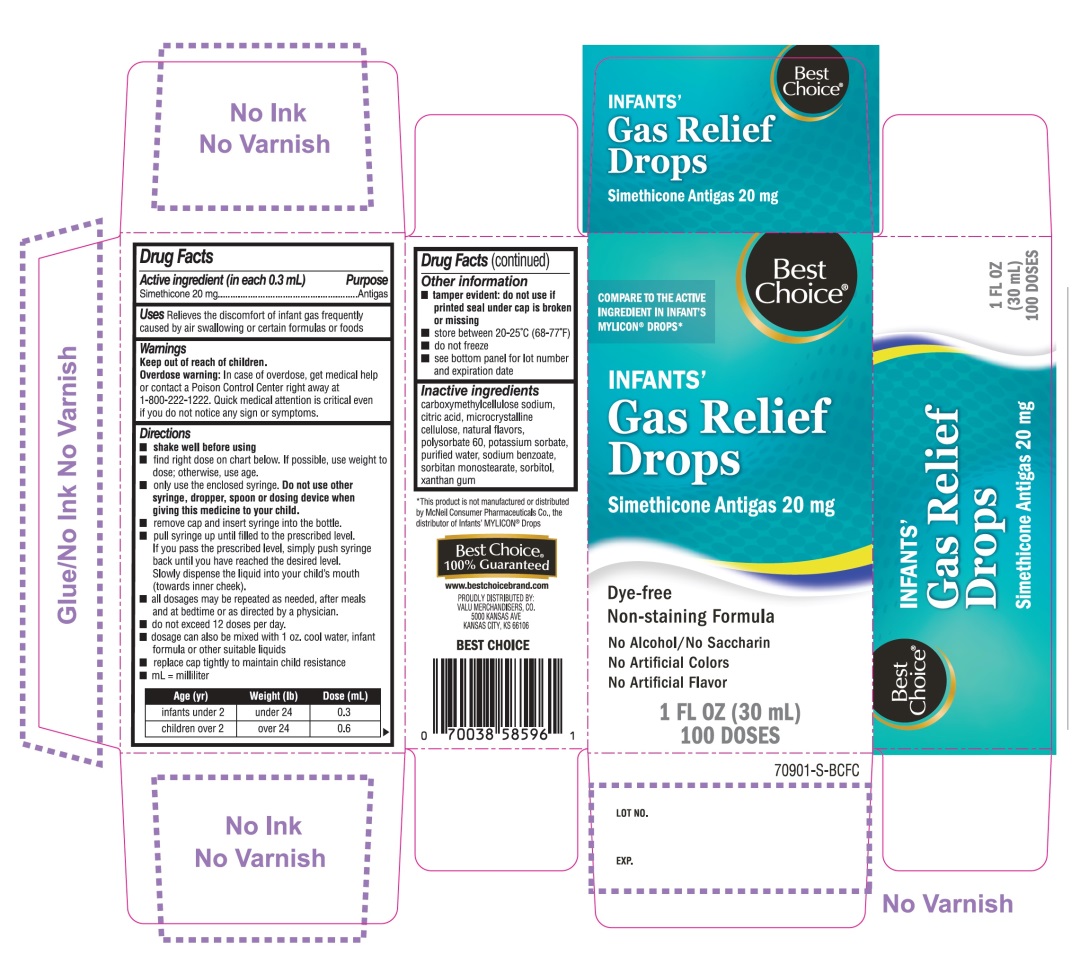 DRUG LABEL: Best Choice
NDC: 63941-709 | Form: SUSPENSION/ DROPS
Manufacturer: BEST CHOICE (VALU MERCHANDISERS COMPANY)
Category: otc | Type: HUMAN OTC DRUG LABEL
Date: 20250716

ACTIVE INGREDIENTS: DIMETHICONE, UNSPECIFIED 20 mg/0.3 mL
INACTIVE INGREDIENTS: CARBOXYMETHYLCELLULOSE SODIUM, UNSPECIFIED; ANHYDROUS CITRIC ACID; MICROCRYSTALLINE CELLULOSE; POLYSORBATE 60; POTASSIUM SORBATE; WATER; SODIUM BENZOATE; SORBITAN MONOSTEARATE; SORBITOL; XANTHAN GUM

Best Choice Infants’ Gas Relief Simethicone Drops

Active ingredient (in each 0.3 mL)

Simethicone 20 mg

Purpose

Antigas

Uses

Relieves the discomfort of infant gas frequently caused by air swallowing or certain formulas or foods

Directions

- shake well before using
- find right dose on chart below. If possible, use weight to dose; otherwise, use age.
- Only use the enclosed syringe. Do not use other syringe, dropper, spoon or dosing device when giving this medicine to your child.
- Remove cap and insert syringe into the bottle.
- Pull syringe up until filled to the prescribed level, simply push syringe back until you have reached the described level. Slowly dispense the liquid into your child’s mouth (towards inner cheek).
- all dosages may be repeated as needed, after meals and at bedtime or as directed by a physician.
- do not exceed 12 doses per day.
- dosage can also be mixed with 1 oz. cool water, infant formula or other suitable liquids.
- Replace cap tightly to maintain child resistance
- mL = milliliter

Age (yr) | Weight (lb) | Dose (mL)
infants under 2 | under 24 | 0.3
children over 2 | over 24 | 0.6

Other information

- tamper evident: do not use if printed seal under cap is broken or missing
- Store between 20-25°C (68-77°F)
- do not freeze
- see bottom panel for lot number and expiration date

Inactive ingredients

carboxymethylcellulose sodium, citric acid, microcrystalline cellulose, natural flavors, polysorbate 60, potassium sorbate, purified water, sodium benzoate, sorbitan monostearate, sorbitol, xanthan gum

Questions or comments?

1-866-467-2748

Principal Display Panel

Best Choice®

COMPARE TO THE ACTIVE INGREDIENT IN INFANTS’ MYLICON®DROPS*

NDC 63941-709-01

INFANTS’

Gas Relief Drops

SIMETHICONE Anti-gas 20 mg

Dye-free

Non-staining formula

- No Alcohol/No Saccharin
- No Artificial Color
- No Artificial Flavor

1 FL OZ (30 mL) 100 DOSES

Best Choice 100% Guaranteed

www.bestchoicebrand.com

PROUDLY DISTRIBUTED BY:

VALU MERCHANDISERS, CO.

5000 KANSAS AVE

KANSAS CITY, KS 66106

BEST CHOICE

*This product is not manufactured or distributed by McNeil Consumer Pharmaceuticals Co., the distributor of Infants’ MYLICON®Drops.